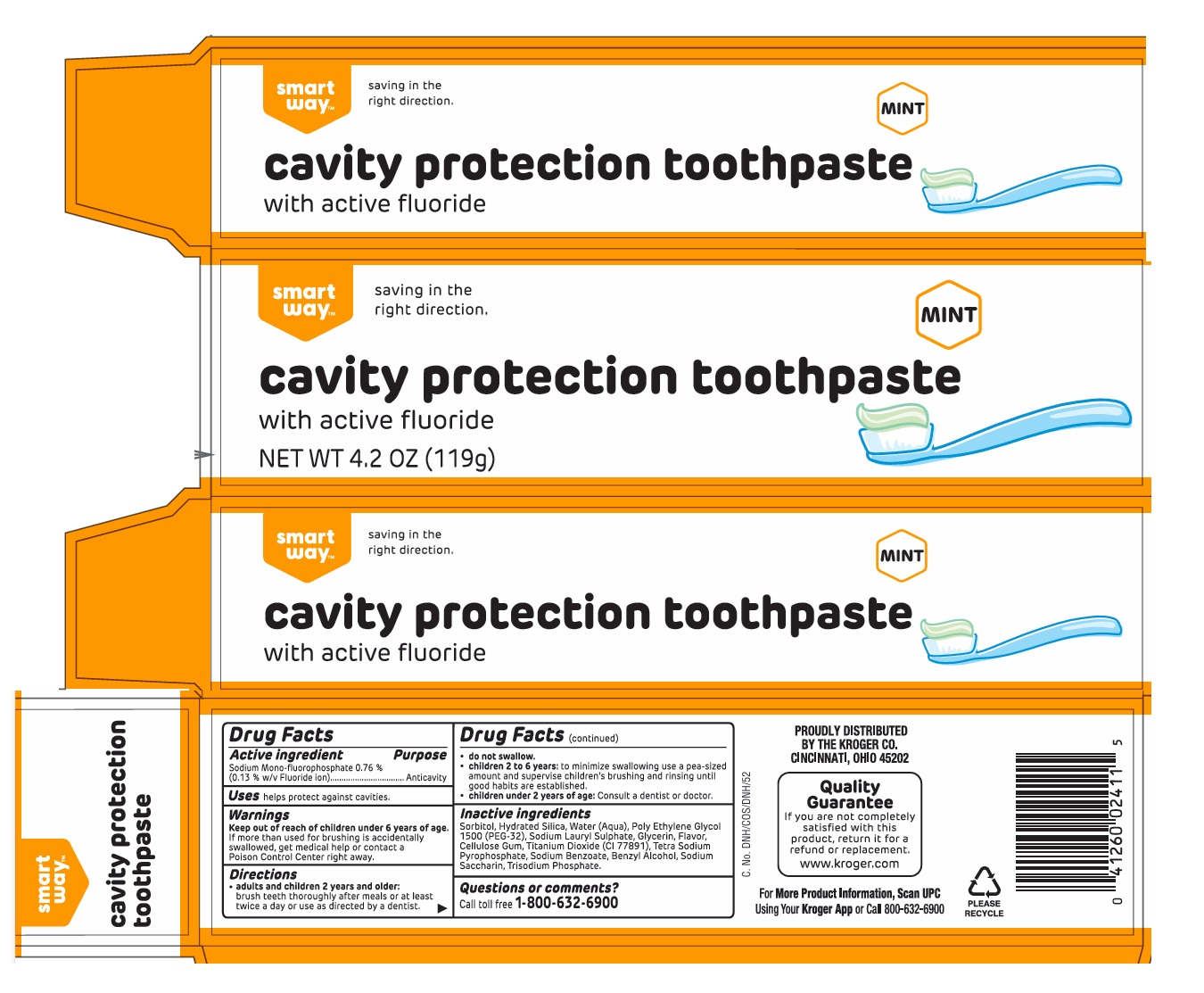 DRUG LABEL: smart way MINT cavity protection
NDC: 59450-010 | Form: PASTE, DENTIFRICE
Manufacturer: The Kroger Co.
Category: otc | Type: HUMAN OTC DRUG LABEL
Date: 20250319

ACTIVE INGREDIENTS: SODIUM MONOFLUOROPHOSPHATE 0.13 g/100 g
INACTIVE INGREDIENTS: SORBITOL; HYDRATED SILICA; WATER; POLYETHYLENE GLYCOL 1600; SODIUM LAURYL SULFATE; GLYCERIN; CARBOXYMETHYLCELLULOSE SODIUM, UNSPECIFIED; TITANIUM DIOXIDE; SODIUM PYROPHOSPHATE; SODIUM BENZOATE; BENZYL ALCOHOL; SACCHARIN SODIUM; SODIUM PHOSPHATE, TRIBASIC, ANHYDROUS

smart way™ cavity protection toothpaste

Active ingredient

Sodium Mono-fluorophosphate 0.76 %
(0.13 % w/v Fluoride ion)

Purpose

Anticavity

Uses

helps protect against cavities.

Warnings

Keep out of reach of children under 6 years of age.
If more than used for brushing is accidentally swallowed, get medical help or contact a Poison Control Center right away.

Directions

• adults and children 2 years and older: brush teeth thoroughly after meals or at least twice a day or use as directed by a dentist.
• do not swallow.
• children 2 to 6 years: to minimize swallowing use a pea-sized amount and supervise children's brushing and rinsing until good habits are established.
• children under 2 years of age: Consult a dentist or doctor.

Inactive ingredients

Sorbitol, Hydrated Silica, Water (Aqua), Poly Ethylene Glycol 1500 (PEG 32), Sodium Lauryl Sulphate, Glycerin, Flavor, Cellulose Gum, Titanium Dioxide (Cl 77891), Tetra Sodium Pyrophosphate, Sodium Benzoate, Benzyl Alcohol, Sodium Saccharin, Trisodium Phosphate

Questions or comments?

Call toll free 1-800-632-6900

saving in the right direction.

with active fluoride

PROUDLY DISTRIBUTED
BY THE KROGER CO.
CINCINNATI, OHIO 45202

Quality Guarantee If you are not completely satisfied with this product, return it for a refund or replacement.

www.kroger.com

For More Product Information, Scan UPC Using Your Kroger App or Call 800-632-6900